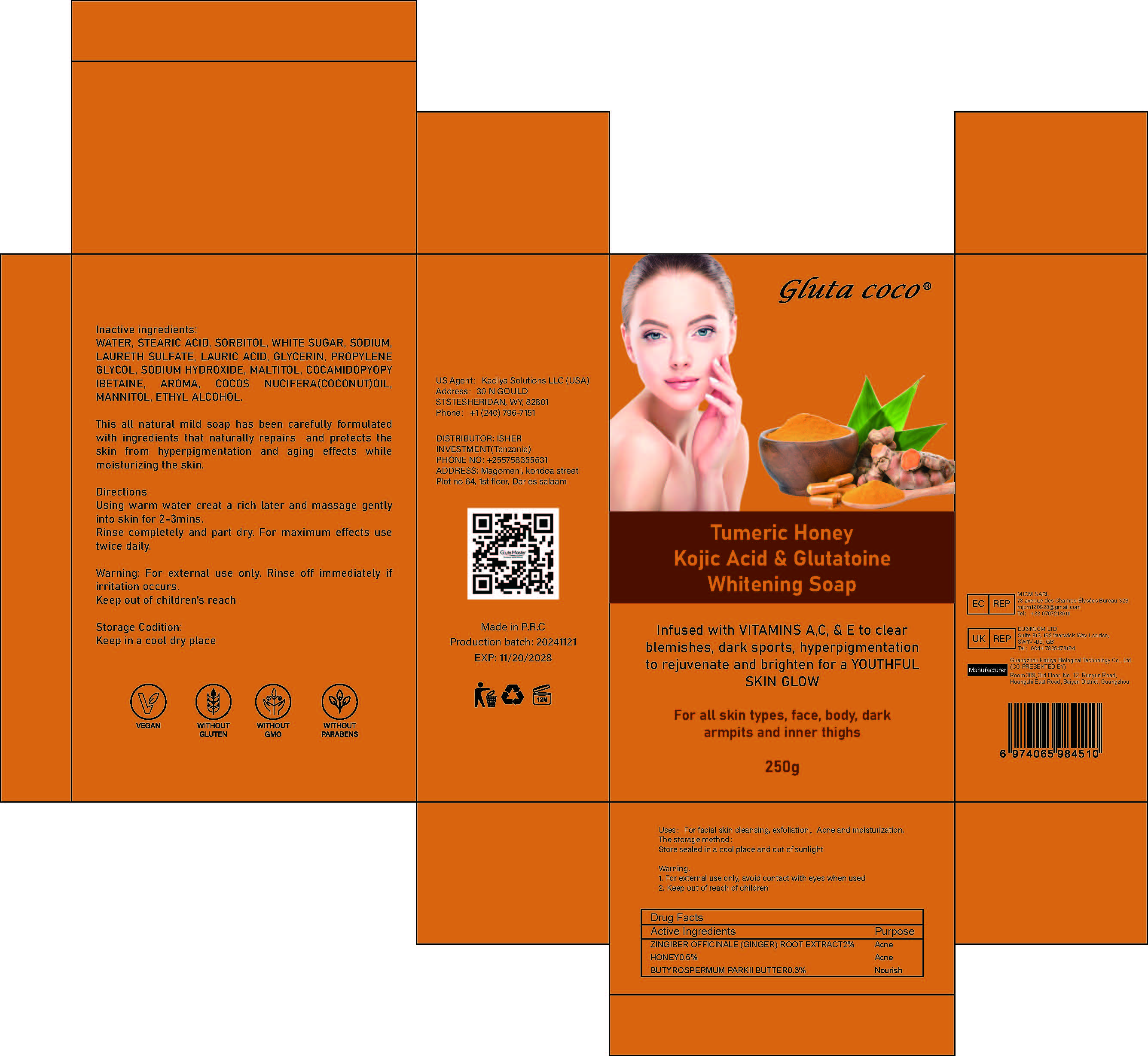 DRUG LABEL: TumericHoneyKojicAcidGlutatoineWhiteningSoap
NDC: 84423-075 | Form: SOAP
Manufacturer: Guangzhou Kadiya Biotechnology Co., Ltd.
Category: otc | Type: HUMAN OTC DRUG LABEL
Date: 20250218

ACTIVE INGREDIENTS: HONEY 1.25 g/250 g; ZINGIBER OFFICINALE (GINGER) ROOT OIL 5 g/250 g; SHEA BUTTER 0.75 g/250 g
INACTIVE INGREDIENTS: MANNITOL; SODIUM HYDROXIDE; PROPYLENE GLYCOL; STEARIC ACID; SUCROSE; LAURIC ACID; MALTITOL; SORBITOL; COCAMIDOPROPYL BETAINE; GLYCERIN; COCONUT; SODIUM LAURETH SULFATE; WATER; ALCOHOL

PURPOSE

For facial skin cleansing, exfoliation，Acne and moisturization

INACTIVE INGREDIENT

WATER、STEARIC ACID、SORBITOL、WHITE SUGAR、SODIUM、
LAURETH SULFATE、LAURIC ACID、GLYCERIN、PROPYLENE GLYCOL、SODIUM HYDROXIDE、MALTITOL、COCAMIDOPYOPY IBETAINE、AROMA、COCOS NUCIFERA(COCONUT)OIL、MANNITOL、ETHYL ALCOHOL

Warning.
1、For external use only, avoid contact with eyes when used
2、Keep out of reach of children

INDICATIONS AND USAGE

This all natural mild soap has been carefully formulated with ingredients that naturally repairs and protects the skin from hyperpigmentation and aging effects while moisturizing the skin.

DOSAGE AND ADMINISTRATION

Using warm water creat a rich later and massage gently into skin for 2-3mins. Rinse completely and part dry. For maximum effects use twice daily.

KEEP OUT OF REACH OF CHILDREN SECTION

Active Ingredients
ZINGIBER OFFICINALE (GINGER) ROOT EXTRACT2%
HONEY0.5%
BUTYROSPERMUM PARKII BUTTER0.3%

PACKAGE LABEL

Active Ingredients
ZINGIBER OFFICINALE (GINGER) ROOT EXTRACT2%
HONEY0.5%
BUTYROSPERMUM PARKII BUTTER0.3%

Uses：
For facial skin cleansing, exfoliation，Acne and moisturization
The storage method：
Store sealed in a cool place and out of sunlight

Warning.
1、For external use only, avoid contact with eyes when used
2、Keep out of reach of children

Inactive ingredients：
WATER、STEARIC ACID、SORBITOL、WHITE SUGAR、SODIUM、
LAURETH SULFATE、LAURIC ACID、GLYCERIN、PROPYLENE GLYCOL、SODIUM HYDROXIDE、MALTITOL、COCAMIDOPYOPY IBETAINE、AROMA、COCOS NUCIFERA(COCONUT)OIL、MANNITOL、ETHYL ALCOHOL